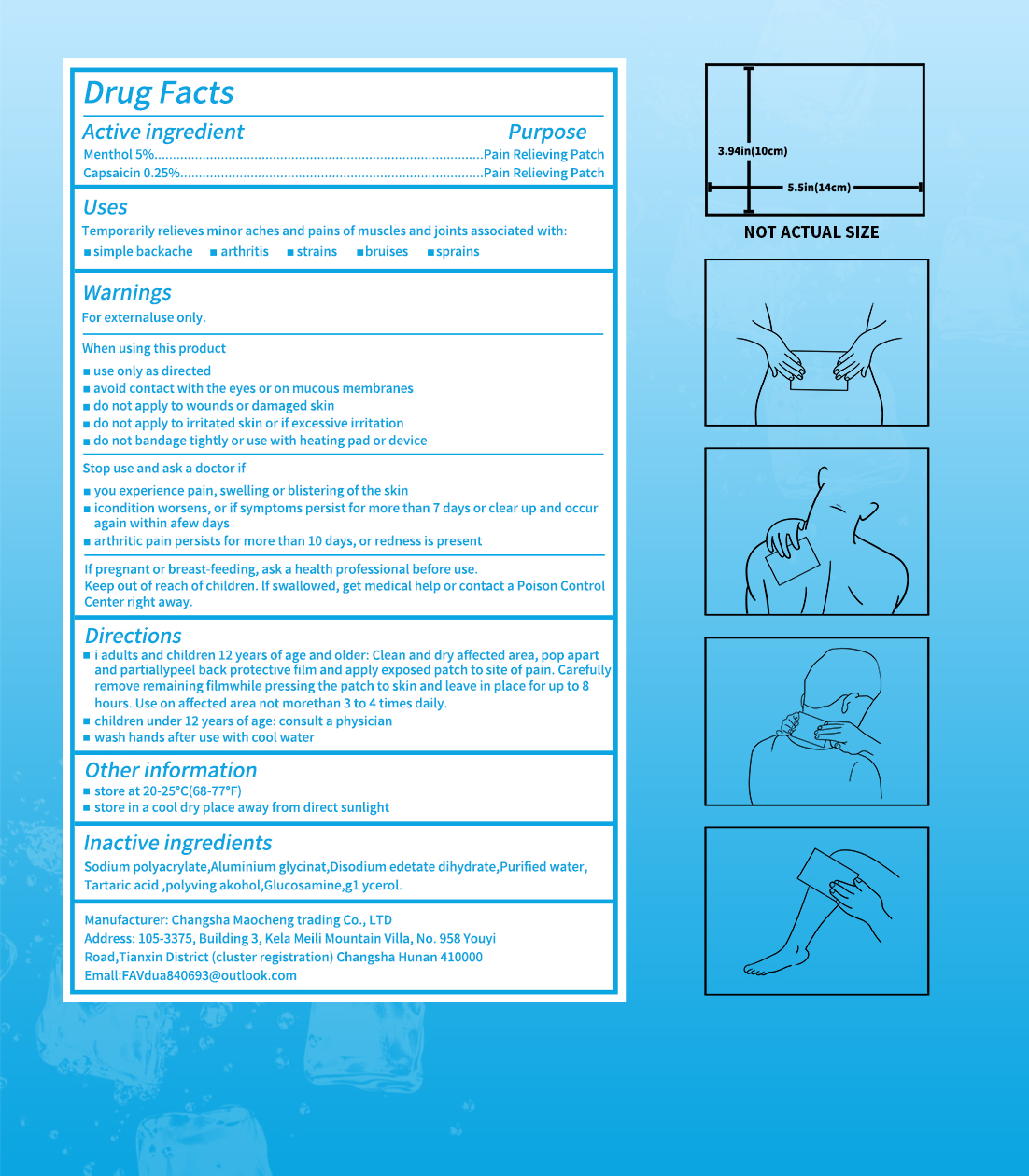 DRUG LABEL: Menthol pain relief patches
NDC: 84876-005 | Form: PATCH
Manufacturer: Menthol pain relief patch
Category: otc | Type: HUMAN OTC DRUG LABEL
Date: 20250802

ACTIVE INGREDIENTS: CAPSAICIN 0.25 g/100 g; MENTHOL 5 g/100 g
INACTIVE INGREDIENTS: SODIUM POLYACRYLATE (2500000 MW); POLYVINYL ALCOHOL; TARTARIC ACID; GLYCERIN; WATER; GLUCOSAMINE; EDETATE DISODIUM; DIHYDROXYALUMINUM AMINOACETATE

ACTIVE INGREDIENT

Menthol 5%
Capsaicin 0.25%.

Uses
Temporarily relieves minor aches and pains of muscles and joints associated with:simple backache, arthritis
,strains,bruises,sprains

WARNINGS

WarningsFor externaluse only.

WHEN USING

use only as directed avoid contact with the eyes or on mucous membranes

do not apply to wounds or damaged skin

do not apply to irritated skin or if excessive irritation

do not bandage tightly or use with heating pad or device

STOP USE

you experience pain, swelling or blistering of the skinicondition worsens, or if symptoms persist for more than 7 days or clear up and occuragain within afew daysarthritic pain persists for more than 10 days, or redness is present

Keep out of reach of children. lfswallowed, get medical help or contact a Poison ControlCenter right away.

INDICATIONS AND USAGE

i adults and children 12 years of age and older: Clean and dry affected area, pop apartand partiallypeel back protective film and apply exposed patch to site of pain. Carefullyremove remaining filmwhile pressing the patch to skin and leave in place for up to 8hours. Use on affected area not morethan 3 to 4 times daily.children under 12 years of age: consult a physicianwash hands after use with cool water

DOSAGE AND ADMINISTRATION

Carefullyremove remaining filmwhile pressing the patch to skin and leave in place for up to 8hours. Use on affected area not morethan 3 to 4 times daily

Inactive ingredients
Sodium polyacrylate,Aluminium glycinat,Disodium edetate dihydrate,Purified water,Tartaric acid ,polyving alcohol,Glucosamine,gl ycerol.